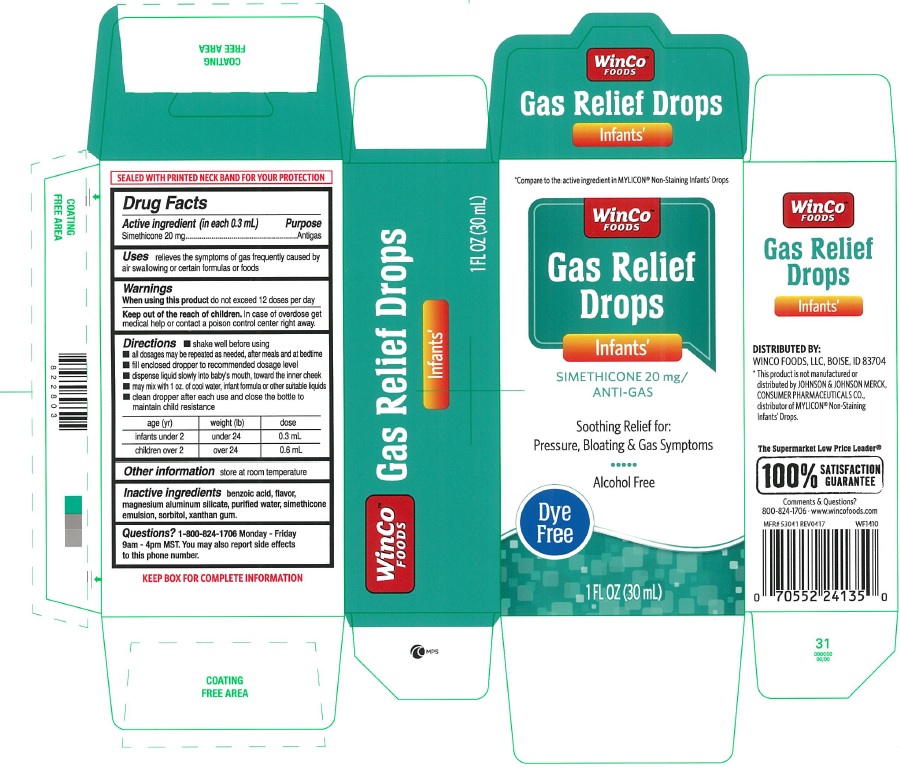 DRUG LABEL: Infants Gas Relief Drops
NDC: 67091-218 | Form: EMULSION
Manufacturer: WinCo Foods, LLC
Category: otc | Type: HUMAN OTC DRUG LABEL
Date: 20191209

ACTIVE INGREDIENTS: DIMETHICONE 20 mg/0.3 mL
INACTIVE INGREDIENTS: SORBITOL; XANTHAN GUM; BENZOIC ACID; MAGNESIUM ALUMINUM SILICATE; WATER

Infants Gas Relief Drops

Active ingredient (in each 0.3 mL)

simethicone 20 mg

Purpose

Antigas

Uses

relieves the symptoms of gas frequently caused by air swallowing or certain formulas or foods

Warnings

When using this product

do not exceed 12 doses per day

Keep out of reach of children. In case of overdose get medical help or contact a poison control center right away.

Directions

- shake well before using
- all dosages may be repeated as needed, after meals and at bedtime
- fill enclosed dropper to recommend dosage level
- dispense liquid slowly into baby's mouth, toward the inner cheek
- may mix with 1 oz. of cool water, infant formula or other suitable liquids
- clean dropper after each use and close the bottle to maintain child resistance

age (yr) | weight (lb) | dose
infants under2 | under 24 | 0.3 mL
children over 2 | over 24 | 0.6 mL

Other information

store at room temperature

Inactive ingredients

benzoic acid, flavor, magnesium aluminum silicate, purified water, simethicone emulsion, sorbitol, xanthan gum

Questions?

1-800-824-1706 Monday - Friday 9am-4pm MST.

You may also report side effects to this phone number

Principal Display Panel

*Compare to the active ingredient in MYLICON® Non-Staining Infants Drops

Infants Gas Relief Drops

SIMETHICONE 20 mg / ANTI-GAS

Soothing Relief for: Pressure, Bloating & Gas Symptoms

Alcohol Free

Dye Free

1 FL OZ (30 mL)